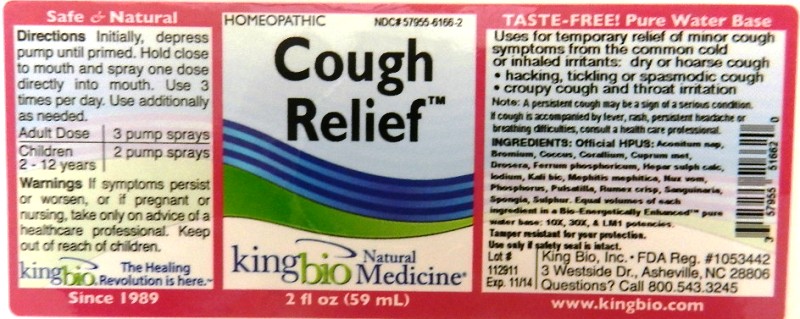 DRUG LABEL: Cough Relief
NDC: 57955-6166 | Form: LIQUID
Manufacturer: King Bio Inc.
Category: homeopathic | Type: HUMAN OTC DRUG LABEL
Date: 20111129

ACTIVE INGREDIENTS: ACONITUM NAPELLUS 10 [hp_X]/59 mL; BROMINE 10 [hp_X]/59 mL; PROTORTONIA CACTI 10 [hp_X]/59 mL; CORALLIUM RUBRUM EXOSKELETON 10 [hp_X]/59 mL; COPPER 10 [hp_X]/59 mL; DROSERA ROTUNDIFOLIA 10 [hp_X]/59 mL; FERROSOFERRIC PHOSPHATE 10 [hp_X]/59 mL; CALCIUM SULFIDE 10 [hp_X]/59 mL; IODINE 10 [hp_X]/59 mL; POTASSIUM DICHROMATE 10 [hp_X]/59 mL; MEPHITIS MEPHITIS ANAL GLAND FLUID 10 [hp_X]/59 mL; STRYCHNOS NUX-VOMICA SEED 10 [hp_X]/59 mL; PHOSPHORUS 10 [hp_X]/59 mL; PULSATILLA VULGARIS 10 [hp_X]/59 mL; RUMEX CRISPUS ROOT 10 [hp_X]/59 mL; SANGUINARIA CANADENSIS ROOT 10 [hp_X]/59 mL; SPONGIA OFFICINALIS SKELETON, ROASTED    10 [hp_X]/59 mL; SULFUR 10 [hp_X]/59 mL
INACTIVE INGREDIENTS: WATER

Cough Relief

Inactive Ingredient

Official HPUS: Aconitum Napellus, Bromium, Coccus Cacti, Corallium Rubrum, Cuprum Metallicum, Drosera Rotundifolia, Ferrum Phosphoricum, Hepar Sulphuris Calcareum, Iodium, Kali Bichromicum, Mephitis Mephitica, Nux Vomica, Phosphorus, Pulsatilla, Rumex Crispus, Sanguinaria Canadensis, Spongia Tosta and Sulphur.

Reference image cough relief.jpg

Inactive Ingredient

Equal volumes of each ingredient in a Bio-Energetically Enhanced pure water base: 10X, 30X, and LM1 potencies.

Reference image cough relief.jpg

Purpose

Uses for temporary relief of minor cough symptoms from the common cold or inhaled irritants: dry or hoarse cough, Hacking, tickling or spasmodic cough, croupy cough and throat irritation.

Note A persistent cough may be a sign of a serious condition. If cough is accompanied by fever, rash, persistent headache or breathing difficulties, consult a health care professional.

Reference image cough relief.jpg

Dosage

Directions Initially, depress pump until primed. Hold close to mouth and spray one dose directly into mouth. Use 3 times per day. use additionally as needed.

Adult Dose 3 pump sprays

Children (2-12 years) 2 pump sprays

Reference image cough relief.jpg

Warnings

If symptoms persist or worsen, or if pregnant or nursing, take only on advice of a healthcare professional. Keep out of reach of children.

Tamper resistant for your protection. Use only if safety seal is intact.

Reference image cough relief.jpg

Keep out of reach of children.

Reference image cough relief.jpg

Indications And Usage

Uses for temporary relief of minor cough symptoms from the common cold or inhaled irritants:

- Dry or hoarse cough
- hacking, tickling or spasmodic cough
- croupy cough and throat irritation

Reference image cough relief.jpg

PACKAGE LABEL

King Bio, Inc.

3 Westside Drive

Asheville, NC 28806

Questions? Call 800.543.3245